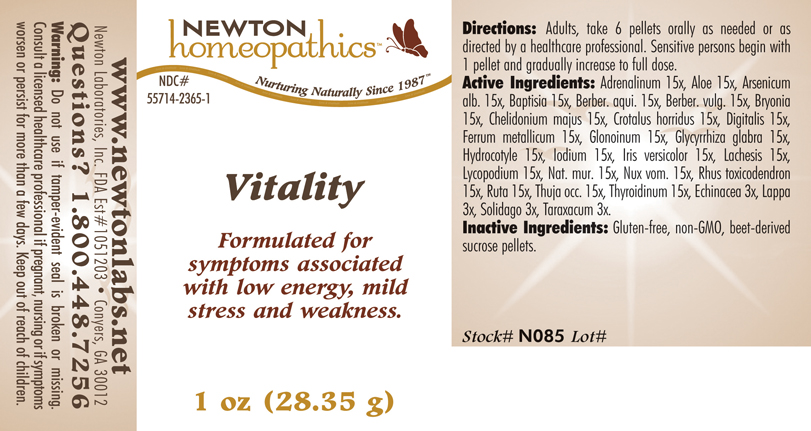 DRUG LABEL: Vitality 
NDC: 55714-2365 | Form: PELLET
Manufacturer: Newton Laboratories, Inc.
Category: homeopathic | Type: HUMAN OTC DRUG LABEL
Date: 20110301

ACTIVE INGREDIENTS: Epinephrine 15 [hp_X]/1 g; Aloe 15 [hp_X]/1 g; Arsenic Trioxide 15 [hp_X]/1 g; Baptisia Tinctoria 15 [hp_X]/1 g; Mahonia Aquifolium Root Bark 15 [hp_X]/1 g; Berberis Vulgaris Root Bark 15 [hp_X]/1 g; Bryonia Alba Root 15 [hp_X]/1 g; Chelidonium Majus 15 [hp_X]/1 g; Crotalus Horridus Horridus Venom 15 [hp_X]/1 g; Digitalis 15 [hp_X]/1 g; Iron 15 [hp_X]/1 g; Nitroglycerin 15 [hp_X]/1 g; Glycyrrhiza Glabra 15 [hp_X]/1 g; Centella Asiatica 15 [hp_X]/1 g; Iodine 15 [hp_X]/1 g; Iris Versicolor Root 15 [hp_X]/1 g; Lachesis Muta Venom 15 [hp_X]/1 g; Lycopodium Clavatum Spore 15 [hp_X]/1 g; Sodium Chloride 15 [hp_X]/1 g; Strychnos Nux-vomica Seed 15 [hp_X]/1 g; Toxicodendron Pubescens Leaf 15 [hp_X]/1 g; Ruta Graveolens Flowering Top 15 [hp_X]/1 g; Thuja Occidentalis Leafy Twig 15 [hp_X]/1 g; Thyroid, Unspecified 15 [hp_X]/1 g; Echinacea, Unspecified 3 [hp_X]/1 g; Arctium Lappa Root 3 [hp_X]/1 g; Solidago Virgaurea Flowering Top 3 [hp_X]/1 g; Taraxacum Officinale 3 [hp_X]/1 g
INACTIVE INGREDIENTS: Sucrose

Vitality

INDICATIONS & USAGE SECTION

Vitality Formulated for symptoms associated with low energy, mild stress and weakness.

DOSAGE & ADMINISTRATION SECTION

Directions: Adults, take 6 pellets orally as needed or as directed by a healthcare professional. Sensitive persons begin with 1 pellet and gradually increase to full dose.

OTC - ACTIVE INGREDIENT SECTION

Adrenalinum 15x, Aloe 15x, Arsenicum alb. 15x, Baptisia 15x, Berber. aqui. 15x, Berber. vulg. 15x, Bryonia 15x, Chelidonium majus 15x, Crotalus horridus 15x, Digitalis 15x, Ferrum metallicum 15x, Glonoinum 15x, Glycyrrhiza glabra 15x, Hydrocotyle 15x, Iodium 15x, Iris versicolor 15x, Lachesis 15x, Lycopodium 15x, Nat. mur. 15x, Nux vom. 15x, Rhus toxicodendron 15x, Ruta 15x, Thuja occ. 15x, Thyroidinum 15x, Echinacea 3x, Lappa 3x, Solidago 3x, Taraxacum 3x.

OTC - PURPOSE SECTION

Formulated for symptoms associated with low energy, mild stress and weakness.

INACTIVE INGREDIENT SECTION

Inactive Ingredients: Gluten-free, non-GMO, beet-derived pellets.

QUESTIONS SECTION

www.newtonlabs.net Newton Laboratories, Inc. FDA Est # 1051203 - Conyers, GA 30012
Questions? 1.800.448.7256

WARNINGS SECTION

Warning: Do not use if tamper - evident seal is broken or missing. Consult a licensed healthcare professional if pregnant, nursing or if symptoms worsen or persist for more than a few days. Keep out of reach of children

OTC - PREGNANCY OR BREAST FEEDING SECTION

Consult a licensed healthcare professional if pregnant, nursing or if symptoms worsen or persist for more than a few days.

OTC - KEEP OUT OF REACH OF CHILDREN SECTION

Keep out of reach of children.